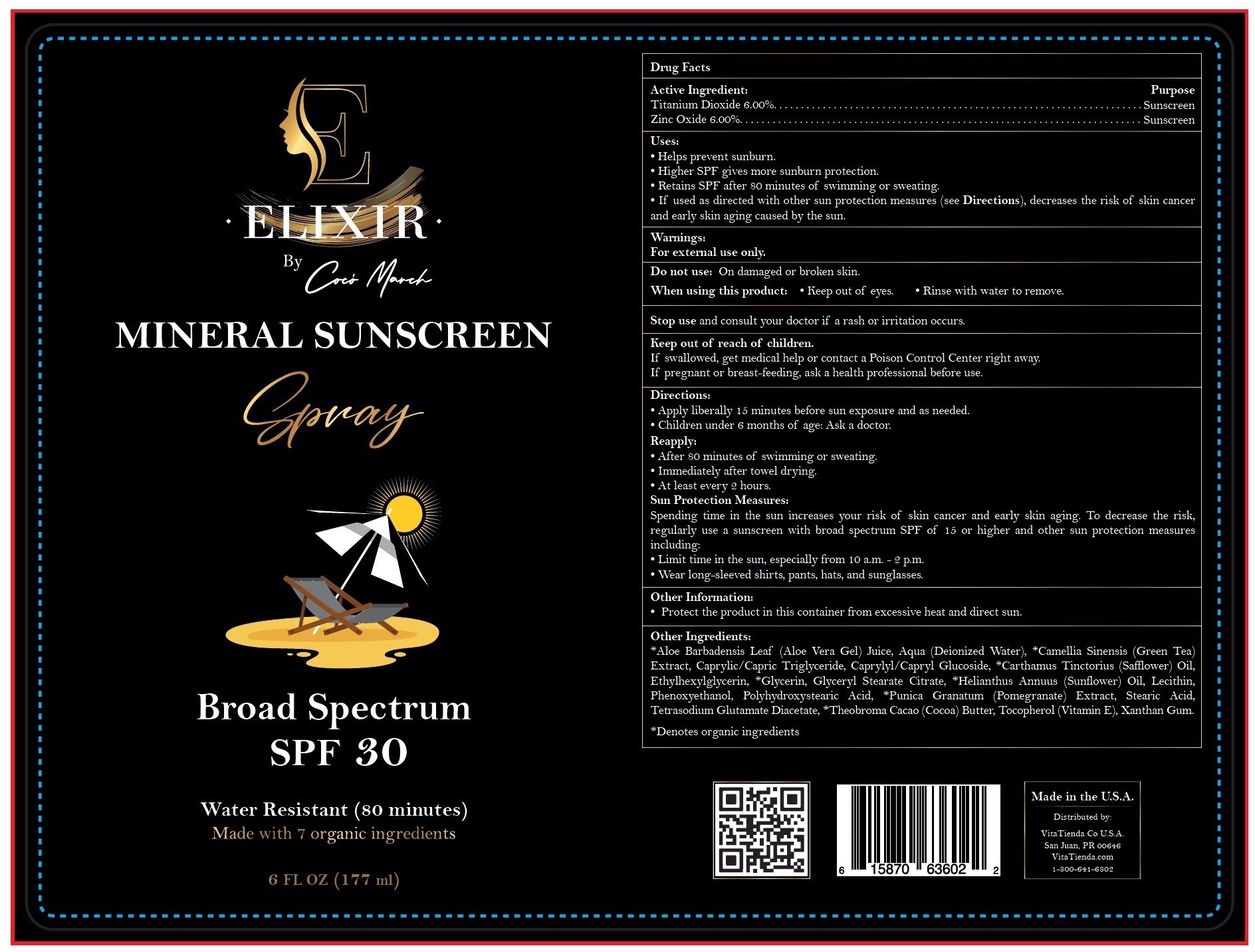 DRUG LABEL: Mineral Sunscreen SPF-30
NDC: 83387-399 | Form: LIQUID
Manufacturer: NEWCO LLC
Category: otc | Type: HUMAN OTC DRUG LABEL
Date: 20231106

ACTIVE INGREDIENTS: TITANIUM DIOXIDE 60 mg/1 mL; ZINC OXIDE 60 mg/1 mL
INACTIVE INGREDIENTS: ALOE VERA LEAF; WATER; GREEN TEA LEAF; MEDIUM-CHAIN TRIGLYCERIDES; CAPRYLYL/CAPRYL OLIGOGLUCOSIDE; SAFFLOWER; ETHYLHEXYLGLYCERIN; GLYCERIN; GLYCERYL STEARATE CITRATE; HELIANTHUS ANNUUS FLOWERING TOP; PHENOXYETHANOL; PUNICA GRANATUM ROOT BARK; STEARIC ACID; TETRASODIUM GLUTAMATE DIACETATE; COCOA; TOCOPHEROL; XANTHAN GUM

ELIXIR Mineral Sunscreen Spray SPF-30

Active Ingredient

Titanium Dioxide 6.00% Zinc Oxide 6.00%

Purpose

Sunscreen

Uses:

• Helps prevent sunburn. • Higher SPF gives more sunburn protection. • Retains SPF after 80 minutes of swimming or sweating. • If used as directed with other sun protection measures (see Directions), decreases the risk of skin cancer and early skin aging caused by the sun.

Warnings:

For external use only.

Do not use:

On damaged or broken skin.

When using this product:

• Keep out of eyes. • Rinse with water to remove.

Stop use and consult your doctor

if a rash or irritation occurs.

Keep out of reach of children.

If swallowed, get medical help or contact a Poison Control Center right away.

If pregnant or breast-feeding,

ask a health professional before use.

Directions:

• Apply liberally 15 minutes before sun exposure and as needed. • Children under 6 months of age: Ask a doctor. • After 80 minutes of swimming or sweating. • Immediately after towel drying. • At least every 2 hours. Spending time in the sun increases your risk of skin cancer and early skin aging. To decrease the risk, regularly use a sunscreen with broad spectrum SPF of 15 or higher and other sun protection measures including: • Limit time in the sun, especially from 10 a.m. - 2 p.m. • Wear long-sleeved shirts, pants, hats, and sunglasses.
Reapply: Sun Protection Measures:

Other Information

• Protect the product in this container from excessive heat and direct sun.

Other Ingredients:

*Aloe Barbadensis Leaf (Aloe Vera Gel) Juice, Aqua (Deionized Water), *Camellia Sinensis (Green Tea) Extract, Caprylic/Capric Triglyceride, Caprylyl/Capryl Glucoside, *Carthamus Tinctorius (Safflower) Oil, Ethylhexylglycerin, *Glycerin, Glyceryl Stearate Citrate, *Helianthus Annuus (Sunflower) Oil, Lecithin, Phenoxyethanol, Polyhydroxystearic Acid, *Punica Granatum (Pomegranate) Extract, Stearic Acid, Tetrasodium Glutamate Diacetate, *Theobroma Cacao (Cocoa) Butter, Tocopherol (Vitamin E), Xanthan Gum.

*Denotes organic ingredients